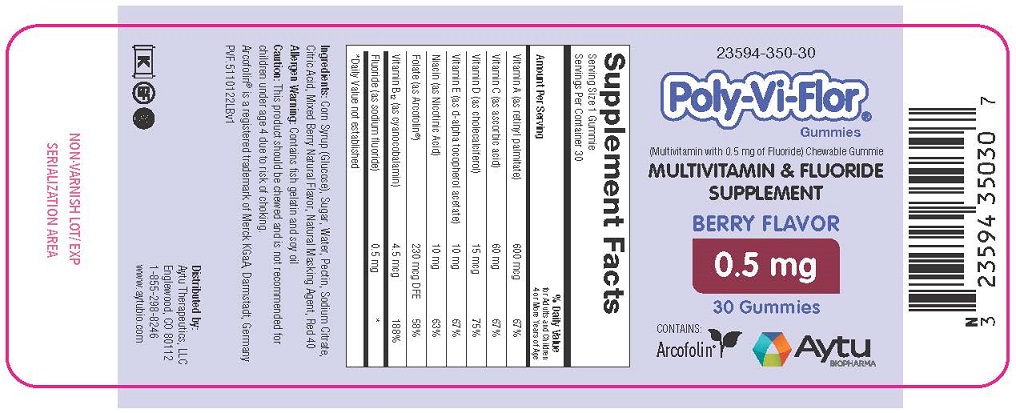 DRUG LABEL: Poly-Vi-Flor Gummies
NDC: 23594-350 | Form: TABLET, CHEWABLE
Manufacturer: Aytu Therapeutics LLC
Category: other | Type: DIETARY SUPPLEMENT
Date: 20221212

ACTIVE INGREDIENTS: VITAMIN A PALMITATE 600 ug/1 1; SODIUM ASCORBATE 60 mg/1 1; CHOLECALCIFEROL 15 ug/1 1; .ALPHA.-TOCOPHEROL, D- 10 mg/1 1; NIACIN 10 mg/1 1; CYANOCOBALAMIN 4.5 ug/1 1; SODIUM FLUORIDE 0.5 mg/1 1; FOLIC ACID 230 ug/1 1
INACTIVE INGREDIENTS: CORN SYRUP; WATER; PECTIN; SODIUM CITRATE; CITRIC ACID MONOHYDRATE

Poly-Vi-Flor Gummies

Poly-Vi-Flor

(Multivitamin with 0.5 mg of Fluoride) Chewable Gummie

Multivitamin and Fluoride Supplement

HEALTH CLAIM

Supplement Facts
Serving Size 1 Gummie
Servings Per Gummie 30
Amount Per Serving |  | % Daily Value for Adults and Children 4 or More Years of Age
Vitamin A (as retinyl palmitate) | 600 mcg | 67%
Vitamin C (as ascorbic acid) | 60 mg | 67%
Vitamin D (as cholecalciferol) | 15 mcg | 75%
Vitamin E (as d-alpha tocopherol acetate) | 10 mg | 67%
Niacin (as Nicotinic Acid) | 10 mg | 63%
Folate (as Arcofolin®) | 230 mcg DFE | 58%
Vitamin B12 (as cyanocobalamin) | 4.5 mcg | 188%
Fluoride (as sodium fluoride) | 0.5 mg | *

*Daily Value not established

Ingredients: Corn Syrup (Glucose), Sugar, Water, Pectin, Sodium Citrate, Citric Acid, Mixed Berry Natural Flavor, Natural Masking Agent, Red 40

Allergen Warning: Contains fish gelatin and soy oil

DOSAGE AND ADMINISTRATION

Caution: This product should be chewed and is not recommended for children under age 4 due to risk of choking.

SAFE HANDLING WARNING

Arcofolin® is a registered trademark of Merck KGaA, Darmstadt, Germany

Distributed by:
Aytu Therapeutics, LLC
Englewood, CO 80112
1-855-298-8246
www.aytubio.com

Principal Display Panel - MultiVitamin with 0.5 MG of Fluoride

23594-350-30

Poly-Vi-Flor®

(Multivitamin with 0.5 mg of Fluoride) Chewable Gummie

MULTIVITAMIN & FLUORIDE SUPPLEMENT

BERRY FLAVOR

0.5 mg

30 Gummies

CONTAINS:ARCOFOLIN

AYTU BIOPHARMA